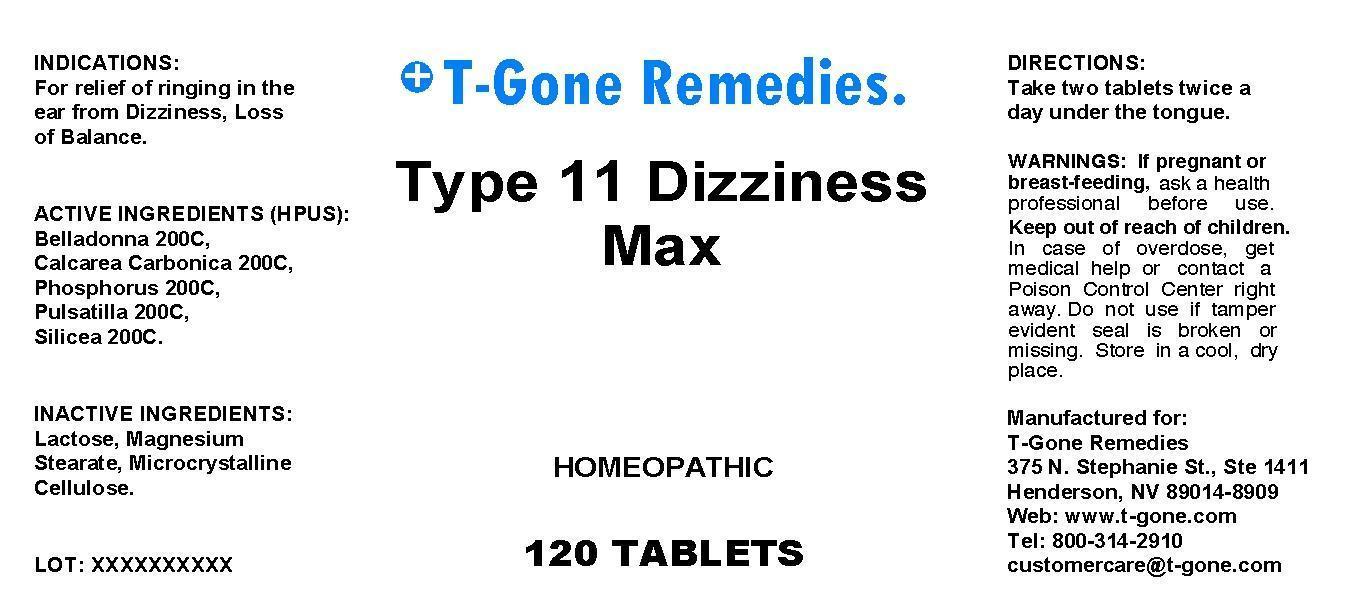 DRUG LABEL: Type 11 Dizziness Max
NDC: 50169-0006 | Form: TABLET
Manufacturer: T-Gone Remedies
Category: homeopathic | Type: HUMAN OTC DRUG LABEL
Date: 20140617

ACTIVE INGREDIENTS: ATROPA BELLADONNA 200 [hp_C]/1 1; OYSTER SHELL CALCIUM CARBONATE, CRUDE 200 [hp_C]/1 1; PHOSPHORUS 200 [hp_C]/1 1; PULSATILLA VULGARIS 200 [hp_C]/1 1; SILICON DIOXIDE 200 [hp_C]/1 1
INACTIVE INGREDIENTS: LACTOSE; MAGNESIUM STEARATE; CELLULOSE, MICROCRYSTALLINE

Drug Facts:

ACTIVE INGREDIENTS:

Belladonna 200X, Calcarea Carbonica 200C, Phosphorus 200C, Pulsatilla (Vulgaris) 200C, Silicea 200C.

INDICATIONS:

For relief of ringing in the ear from Dizziness, Loss of Balance.

WARNINGS:

If pregnant or breast-feeding, ask a health professional before use.

Keep out of reach of children. In case of overdose, get medical help or contact a Poison Control Center right away.

Do not use if tamper evident seal is broken or missing.

Store in a cool, dry place.

Keep out of reach of children. In case of overdose, get medical help or contact a Poison Control Center right away.

DIRECTONS:

Take two tablets twice a day under the tongue.

INDICATIONS:

For relief of ringing in the ear from Dizziness, Loss of Balance.

INACTIVE INGREDIENTS:

Lactose, Mangesium stearate, Microcrystalline cellulose.

QUESTIONS:

Manufactured for:

T-Gone Remedies

375 N. Stephanie St., Ste 1411

Henderson, NV 89014-8909

Web: www.t-gone.com

Tel: 800-314-2910

customercare@t-gone.com

PACKAGE LABEL DISPLAY:

T-Gone Remedies.

Type 11 Dizziness Max

HOMEOPATHIC

120 TABLETS